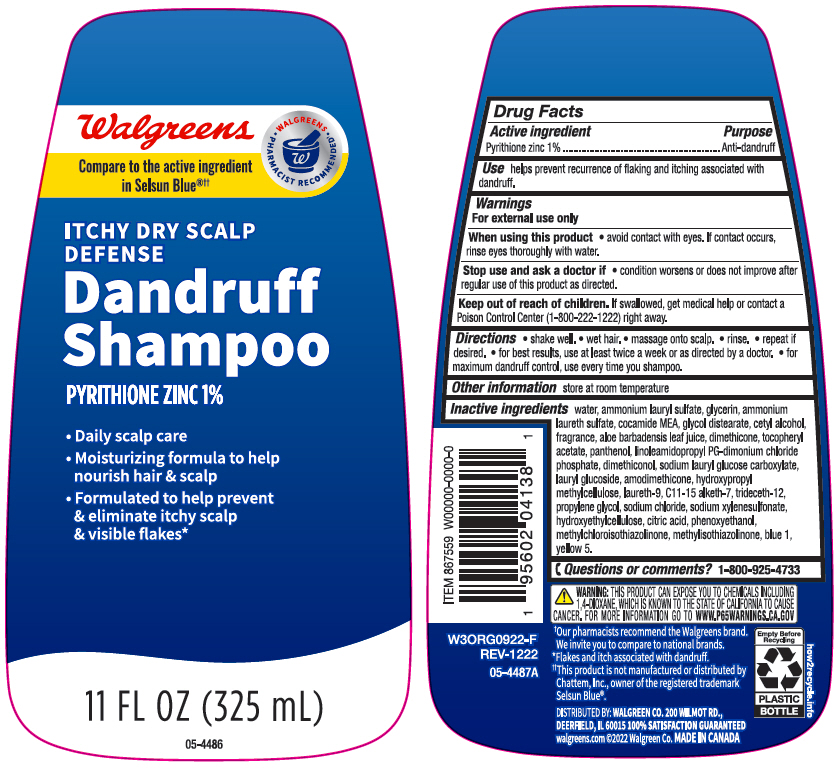 DRUG LABEL: Walgreens Dandruff Itchy Dry Scalp Defense
NDC: 0363-4138 | Form: SHAMPOO
Manufacturer: Walgreen Company
Category: otc | Type: HUMAN OTC DRUG LABEL
Date: 20241101

ACTIVE INGREDIENTS: Pyrithione Zinc 10 mg/1 mL
INACTIVE INGREDIENTS: Water; Ammonium Lauryl Sulfate; Glycerin; COCO MONOETHANOLAMIDE; Glycol Distearate; Cetyl Alcohol; ALOE VERA LEAF; Dimethicone; .ALPHA.-TOCOPHEROL ACETATE, DL-; Panthenol; LINOLEAMIDOPROPYL PROPYLENE GLYCOL-DIMONIUM CHLORIDE PHOSPHATE; DIMETHICONOL (2000 CST); Lauryl Glucoside; AMODIMETHICONE (800 CST); HYPROMELLOSE, UNSPECIFIED; POLIDOCANOL; C11-15 ALKETH-7; Trideceth-12; Propylene Glycol; Sodium Chloride; Sodium Xylenesulfonate; HYDROXYETHYL CELLULOSE, UNSPECIFIED; CITRIC ACID MONOHYDRATE; Phenoxyethanol; Methylchloroisothiazolinone; Methylisothiazolinone; FD&C BLUE NO. 1; FD&C YELLOW NO. 5

Walgreens Dandruff Shampoo Itchy Dry Scalp Defense
Anti-dandruff

Drug Facts

Active ingredient

Pyrithione Zinc 1%

Purpose

Anti-dandruff

Use

helps prevent recurrence of flaking and itching associated with dandruff.

Warnings

For external use only

When using this product

- avoid contact with the eyes. If contact occurs, rinse eyes thoroughly with water.

Stop use and ask a doctor if

- condition worsens or does not improve after regular use as directed.

Keep out of reach of children. If swallowed, get medical help or contact a Poison Control Center (1-800-222-1222) right away.

Directions

- shake well
- wet hair
- massage onto scalp
- rinse
- repeat if desired
- for best results use at least twice a week or as directed by a doctor
- for maximum dandruff control, use every time you shampoo.

Other information

store at room temperature

Inactive ingredients

water, ammonium lauryl sulfate, glycerin, ammonium laureth sulfate, cocamide MEA, glycol distearate, cetyl alcohol, fragrance, aloe barbadensis leaf juice, dimethicone, tocopheryl acetate, panthenol, linoleamidopropyl PG-dimonium chloride phosphate, dimethiconol, sodium lauryl glucose carboxylate, lauryl glucoside, amodimethicone, hydroxypropyl methylcellulose, laureth-9, C11-15 alketh-7, trideceth-12, propylene glycol, sodium chloride, sodium xylenesulfonate, hydroxyethylcellulose, citric acid, phenoxyethanol, methylchloroisothiazolinone, methylisothiazolinone, blue 1, yellow 5.

Questions or Comments?

1-800-925-4733

STOP USE

DISTRIBUTED BY: WALGREEN CO. 200 WILMOT RD.,
DEERFIELD, IL 60015

PRINCIPAL DISPLAY PANEL - 325 mL Bottle Label

Walgreens

• WALGREENS •
PHARMACIST RECOMMENDED†

Compare to the active ingredient
in Selsun Blue®††

ITCHY DRY SCALP
DEFENSE

Dandruff
Shampoo

PYRITHIONE ZINC 1%

- Daily scalp care
- Moisturizing formula to help
  nourish hair & scalp
- Formulated to help prevent
  & eliminate itchy scalp
  & visible flakes*

11 FL OZ (325 mL)

05-4486